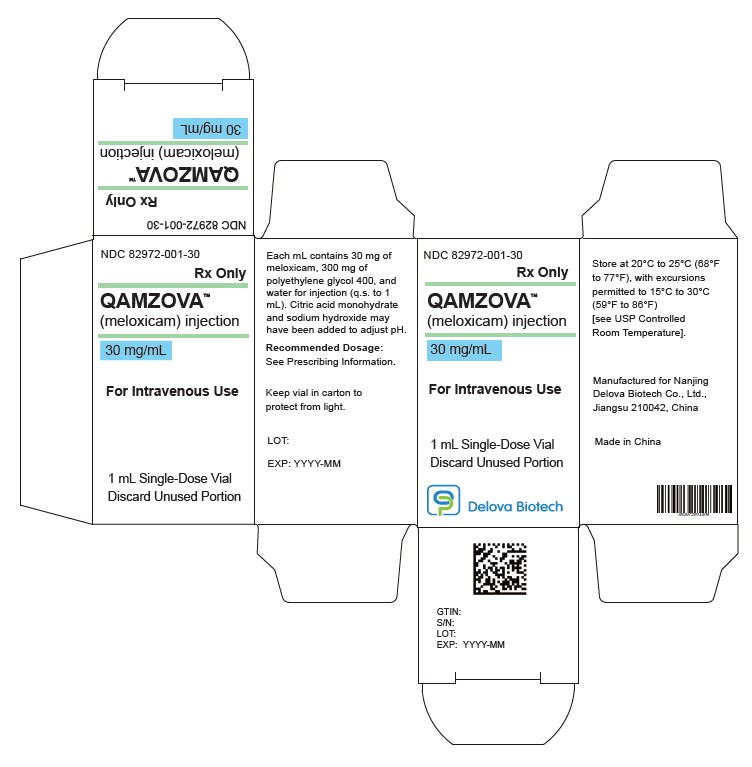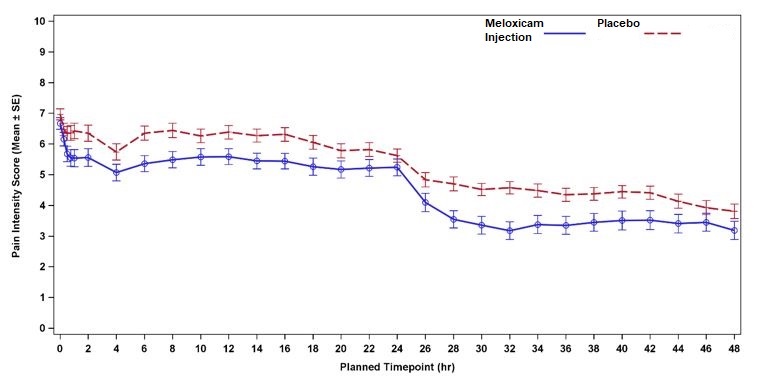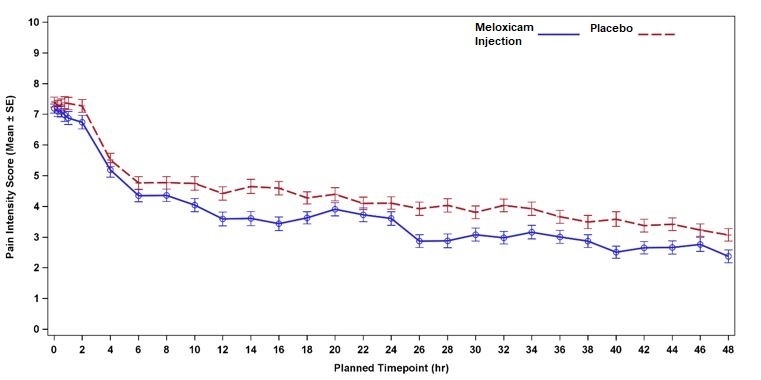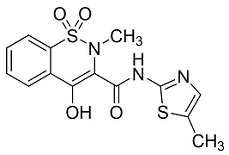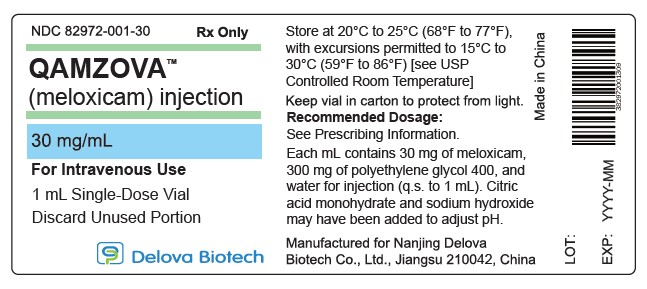 DRUG LABEL: QAMZOVA
NDC: 82972-001 | Form: INJECTION
Manufacturer: Nanjing Delova Biotech Co., Ltd.
Category: prescription | Type: HUMAN PRESCRIPTION DRUG LABEL
Date: 20250423

ACTIVE INGREDIENTS: MELOXICAM 30 mg/1 mL
INACTIVE INGREDIENTS: POLYETHYLENE GLYCOL 400 300 mg/1 mL; SODIUM HYDROXIDE; CITRIC ACID MONOHYDRATE

HIGHLIGHTS OF PRESCRIBING INFORMATION

These highlights do not include all the information needed to use QAMZOVATMsafely and effectively. See full prescribing information for QAMZOVA.
QAMZOVA (meloxicam injection), for intravenous use
Initial U.S. Approval: 2000

WARNING: RISK OF SERIOUS CARDIOVASCULAR AND GASTROINTESTINAL EVENTS

See full prescribing information for complete boxed warning.

- Non-steroidal anti-inflammatory drugs (NSAIDs) cause an increased risk of serious cardiovascular thrombotic events, including myocardial infarction, and stroke, which can be fatal. This risk may occur early in treatment and may increase with duration of use. (5.1)
- QAMZOVA is contraindicated in the setting of coronary artery bypass graft (CABG) surgery. (4, 5.1)
- NSAIDs cause an increased risk of serious gastrointestinal (GI) adverse events including bleeding, ulceration, and perforation of the stomach or intestines, which can be fatal. These events can occur at any time during use and without warning symptoms. Elderly patients and patients with a prior history of peptic ulcer disease and/or GI bleeding are at greater risk for serious GI events. (5.2)

1 INDICATIONS AND USAGE

QAMZOVA contains meloxicam, which is an NSAID, and is indicated for use in adults for the management of moderate-to-severe pain, alone or in combination with non-NSAID analgesics.

Limitation of Use

Because of delayed onset of analgesia, QAMZOVA alone is not recommended for use when rapid onset of analgesia is required. (1)

2 DOSAGE AND ADMINISTRATION

- Use for the shortest duration consistent with individual patient treatment goals. (2)
- The recommended dose is 30 mg once daily, administered by intravenous bolus injection over 15 seconds. (2)
- Monitor patient analgesic response and administer a short-acting, non-NSAID, immediate-release analgesic if response is inadequate. (2)
- Patients must be well hydrated before QAMZOVA administration. (2)

3 DOSAGE FORMS AND STRENGTHS

QAMZOVA (meloxicam) injection, single-dose vial containing 30 mg/mL per vial. (3)

4 CONTRAINDICATIONS

- Known hypersensitivity to meloxicam or any components of the drug product. (4)
- History of asthma, urticaria, or other allergic-type reactions after taking aspirin or other NSAIDs. (4)
- In the setting of coronary artery bypass graft (CABG) surgery. (4)
- Moderate to severe renal insufficiency patients who are at risk for renal failure due to volume depletion. (4)

5 WARNINGS AND PRECAUTIONS

- Hepatotoxicity: Inform patients of warning signs and symptoms of hepatotoxicity. Discontinue QAMZOVA immediately if abnormal liver tests persist or worsen or if clinical signs and symptoms of liver disease develop. (5.3)
- Hypertension: Patients taking some antihypertensive medications may have impaired response to these therapies when taking QAMZOVA. Monitor blood pressure. (5.4, 7)
- Heart Failure and Edema: Avoid use of QAMZOVA in patients with severe heart failure unless benefits are expected to outweigh risk of worsening heart failure. (5.5)
- Renal Toxicity: Monitor renal function in patients with renal or hepatic impairment, heart failure, dehydration, or hypovolemia. Avoid use of QAMZOVA in patients with advanced renal disease unless benefits are expected to outweigh risk of worsening renal function. (5.6)
- Anaphylactic Reactions: Seek emergency help if an anaphylactic reaction occurs. (5.7)
- Exacerbation of Asthma Related to Aspirin Sensitivity: QAMZOVA is contraindicated in patients with aspirin-sensitive asthma. Monitor patients with preexisting asthma (without aspirin sensitivity). (5.8)
- Serious Skin Reactions: Discontinue QAMZOVA at first appearance of skin rash or other signs of hypersensitivity. (5.9)
- Drug Reaction with Eosinophilia and Systemic Symptoms (DRESS): Discontinue and evaluate clinically. (5.10)
- Hematologic Toxicity: Monitor hemoglobin or hematocrit in patients with any signs or symptoms of anemia. (5.12, 7)
- Fetal Toxicity: Limit use of NSAIDs, including QAMZOVA, between about 20 to 30 weeks in pregnancy due to the risk of oligohydramnios/fetal renal dysfunction. Avoid use of NSAIDs in women at about 30 weeks gestation and later in pregnancy due to the risks of oligohydramnios/fetal renal dysfunction and premature closure of the fetal ductus arteriosus. (5.11, 8.1)

6 ADVERSE REACTIONS

The most common adverse reactions (≥ 2% and greater than placebo) in controlled clinical trials include constipation, GGT increased, and anemia. (6)

To report SUSPECTED ADVERSE REACTIONS, contact Nanjing Delova Biotech Co., Ltd. at 1-844-406-8288 or FDA at 1-800-FDA-1088 or www.fda.gov/medwatch.

7 DRUG INTERACTIONS

- Drugs that Interfere with Hemostasis (e.g., warfarin, aspirin, SSRIs/SNRIs): Monitor patients for bleeding who are concomitantly taking QAMZOVA with drugs that interfere with hemostasis. Concomitant use of QAMZOVA and analgesic doses of aspirin is not generally recommended. (7)
- ACE Inhibitors, Angiotensin Receptor Blockers (ARBs), or Beta-Blockers: Concomitant use with QAMZOVA may diminish the antihypertensive effect of these drugs. Monitor blood pressure. (7)
- ACE Inhibitors and ARBs: Concomitant use with QAMZOVA in elderly, volume-depleted, or those with renal impairment may result in deterioration of renal function. In such high risk patients, monitor for signs of worsening renal function. (7)
- Diuretics: NSAIDs can reduce natriuretic effect of furosemide and thiazide diuretics. Monitor patients to assure diuretic efficacy including antihypertensive effects. (7)

8 USE IN SPECIFIC POPULATIONS

- Infertility: NSAIDs are associated with reversible infertility. Consider withdrawal of QAMZOVA in women who have difficulties conceiving. (8.3)

FULL PRESCRIBING INFORMATION

WARNING: RISK OF SERIOUS CARDIOVASCULAR AND GASTROINTESTINAL EVENTS

Cardiovascular Risk

- Non-steroidal anti-inflammatory drugs (NSAIDs) cause an increased risk of serious cardiovascular thrombotic events including myocardial infarction and stroke, which can be fatal. This risk may occur early in treatment and may increase with duration of use [ see Warnings and Precautions (5.1) ].
- QAMZOVA is contraindicated in the setting of coronary artery bypass graft (CABG) surgery [ see Contraindications (4) and Warnings and Precautions (5.1) ].

Gastrointestinal Risk

- NSAIDs cause an increased risk of serious gastrointestinal (GI) adverse events including bleeding, ulceration, and perforation of the stomach or intestines, which can be fatal. These events can occur at any time during us e and without warning symptoms. Elderly patients and patients with a prior history of peptic ulcer disease and/or GI bleeding are at greater risk for serious GI events [ see Warnings and Precautions (5.2) ].

1 INDICATIONS AND USAGE

QAMZOVA is indicated for use in adults for the management of moderate-to-severe pain, alone or in combination with non-NSAID analgesics.

Limitation of Use
Because of delayed onset of analgesia, QAMZOVA alone is not recommended for use when rapid onset of analgesia is required.

2 DOSAGE AND ADMINISTRATION

Use for the shortest duration consistent with individual patient treatment goals [ see Warnings and Precautions (5) ].

For intravenous administration only.

The recommended dose of QAMZOVA is 30 mg once daily, administered by intravenous bolus injection over 15 seconds.

When initiating QAMZOVA, monitor patient analgesic response. Because the median time to meaningful pain relief was 2 and 3 hours after meloxicam injection administration in two clinical studies, a non-NSAID analgesic with a rapid onset of effect may be needed, for example, upon anesthetic emergence or resolution of local or regional anesthetic blocks [ see Clinical Studies (14)] .

Some patients may not experience adequate analgesia for the entire 24-hour dosing interval and may require administration of a short-acting, non-NSAID, immediate-release analgesic [ see Clinical Studies (14) ].

To reduce the risk of renal toxicity, patients must be well hydrated prior to administration of QAMZOVA.

Visually inspect parenteral drug products for particulate matter and discoloration prior to administration. Should the contents appear discolored or contain particulate matter, discard the vial [ see Dosage Forms and Strengths (3) ].

3 DOSAGE FORMS AND STRENGTHS

QAMZOVA (meloxicam) injection is a sterile, clear, greenish-yellow, non-pyrogenic, aqueous solution intended for intravenous use available as a clear, single-dose vial containing 30 mg/mL per vial.

4 CONTRAINDICATIONS

QAMZOVA is contraindicated in the following patients:

- Known hypersensitivity (e.g., anaphylactic reactions and serious skin reactions) to meloxicam or any components of the drug product [ see Warnings and Precautions (5.7) ].
- History of asthma, urticaria, or other allergic-type reactions after taking aspirin or other NSAIDs. Severe, sometimes fatal anaphylactic-like reactions to NSAIDs have been reported in such patients [ see Warnings and Precautions (5.8) ].
- In the setting of coronary artery bypass graft (CABG) surgery [ see Warnings and Precautions (5.1) ].
- Moderate to severe renal insufficiency patients who are at risk for renal failure due to volume depletion [ see Warnings and Precautions (5.6) ].

5 WARNINGS AND PRECAUTIONS

5.1 Cardiovascular Thrombotic Events

Clinical trials of several COX-2 selective and nonselective NSAIDs of up to three years duration have shown an increased risk of serious cardiovascular (CV) thrombotic events, including myocardial infarction (MI) and stroke, which can be fatal. Based on available data, it is unclear that the risk for CV thrombotic events is similar for all NSAIDs. The relative increase in serious CV thrombotic events over baseline conferred by NSAID use appears to be similar in those with and without known CV disease or risk factors for CV disease. However, patients with known CV disease or risk factors had a higher absolute incidence of excess serious CV thrombotic events, due to their increased baseline rate. Some observational studies found that this increased risk of serious CV thrombotic events began as early as the first weeks of treatment. The increase in CV thrombotic risk has been observed most consistently at higher doses.

To minimize the potential risk for an adverse CV event in NSAID-treated patients, use the lowest effective dose for the shortest duration possible. Physicians and patients should remain alert for the development of such events, throughout the entire treatment course, even in the absence of previous CV symptoms. Patients should be informed about the symptoms of serious CV events and the steps to take if they occur.

There is no consistent evidence that concurrent use of aspirin mitigates the increased risk of serious CV thrombotic events associated with NSAID use. The concurrent use of aspirin and an NSAID, such as meloxicam, increases the risk of serious gastrointestinal (GI) events [ see Warnings and Precautions (5.2) ].

Status Post Coronary Artery Bypass Graft (CABG) Surgery
Two large, controlled clinical trials of a COX-2 selective NSAID for the treatment of pain in the first 10-14 days following CABG surgery found an increased incidence of myocardial infarction and stroke. NSAIDs are contraindicated in the setting of CABG [ see Contraindications (4) ].

Post-MI Patients
Observational studies conducted in the Danish National Registry have demonstrated that patients treated with NSAIDs in the post-MI period were at increased risk of reinfarction, CV-related death, and all-cause mortality beginning in the first week of treatment. In this same cohort, the incidence of death in the first year post-MI was 20 per 100 person years in NSAID-treated patients compared to 12 per 100 person years in non-NSAID exposed patients. Although the absolute rate of death declined somewhat after the first year post-MI, the increased relative risk of death in NSAID users persisted over at least the next four years of follow-up.

Avoid the use of QAMZOVA in patients with a recent MI unless the benefits are expected to outweigh the risk of recurrent CV thrombotic events. If QAMZOVA is used in patients with a recent MI, monitor patients for signs of cardiac ischemia.

5.2 Gastrointestinal Effects- Risk of Ulceration, Bleeding, and Perforation

NSAIDs, including meloxicam, can cause serious gastrointestinal (GI) adverse events including inflammation, bleeding, ulceration, and perforation of the esophagus, stomach, small intestine, or large intestine, which can be fatal. These serious adverse events can occur at any time, with or without warning symptoms, in patients treated with QAMZOVA. Only one in five patients who develop a serious upper GI adverse event on NSAID therapy is symptomatic. Upper GI ulcers, gross bleeding, or perforation caused by NSAIDs occurred in approximately 1% of patients treated for 3-6 months, and in about 2-4% of patients treated for one year. However, even short-term NSAID therapy is not without risk.

Risk Factors for GI Bleeding, Ulceration, and Perforation
Patients with a prior history of peptic ulcer disease and/or GI bleeding who used NSAIDs had a greater than 10-fold increased risk for developing a GI bleed compared to patients without these risk factors. Other factors that increase the risk of GI bleeding in patients treated with NSAIDs include longer duration of NSAID therapy; concomitant use of oral corticosteroids, aspirin, anticoagulants, or selective serotonin reuptake inhibitors (SSRIs); smoking; use of alcohol; older age; and poor general health status. Most postmarketing reports of fatal GI events occurred in elderly or debilitated patients. Additionally, patients with advanced liver disease and/or coagulopathy are at increased risk for GI bleeding.

Strategies to Minimize the GI Risks in NSAID-treated patients:

- Use the lowest effective dosage for the shortest possible duration.
- Avoid administration of more than one NSAID at a time.
- Avoid use in patients at higher risk unless benefits are expected to outweigh the increased risk of bleeding. For such patients, as well as those with active GI bleeding, consider alternate therapies other than NSAIDs.
- Remain alert for signs and symptoms of GI ulceration and bleeding during NSAID therapy.
- If a serious GI adverse event is suspected, promptly initiate evaluation and treatment, and discontinue QAMZOVA until a serious GI adverse event is ruled out.
- In the setting of concomitant use of low-dose aspirin for cardiac prophylaxis, monitor patients more closely for evidence of GI bleeding [ see Drug Interactions (7) ].

5.3 Hepatotoxicity

Elevations of ALT or AST (three or more times the upper limit of normal [ULN]) have been reported in approximately 1% of NSAID-treated patients in clinical trials. In addition, rare, sometimes fatal, cases of severe hepatic injury, including fulminant hepatitis, liver necrosis, and hepatic failure have been reported.

Elevations of ALT or AST (less than three times ULN) may occur in up to 15% of patients treated with NSAIDs including meloxicam.

Inform patients of the warning signs and symptoms of hepatotoxicity (e.g., nausea, fatigue, lethargy, diarrhea, pruritus, jaundice, right upper quadrant tenderness, and "flu-like" symptoms). If clinical signs and symptoms consistent with liver disease develop, or if systemic manifestations occur (e.g., eosinophilia, rash, etc.), discontinue QAMZOVA immediately, and perform a clinical evaluation of the patient [ see Use in Specific Populations (8.6) and Clinical Pharmacology (12.3) ].

5.4 Hypertension

NSAIDs, including QAMZOVA, can lead to new onset of hypertension or worsening of pre-existing hypertension, either of which may contribute to the increased incidence of CV events. Patients taking angiotensin converting enzyme (ACE) inhibitors, thiazides or loop diuretics may have impaired response to these therapies when taking NSAIDs [ see Drug Interactions (7) ].

Monitor blood pressure (BP) during the initiation of NSAID treatment and throughout the course of therapy.

5.5 Heart Failure and Edema

The Coxib and traditional NSAID Trialists’ Collaboration meta-analysis of randomized controlled trials demonstrated an approximately two-fold increase in hospitalizations for heart failure in COX-2 selective-treated patients and nonselective NSAID-treated patients compared to placebo-treated patients. In a Danish National Registry study of patients with heart failure, NSAID use increased the risk of MI, hospitalization for heart failure, and death.

Additionally, fluid retention and edema have been observed in some patients treated with NSAIDs. Use of meloxicam may blunt the CV effects of several therapeutic agents used to treat these medical conditions (e.g., diuretics, ACE inhibitors, or angiotensin receptor blockers [ARBs]) [ see Drug Interactions (7) ].

Avoid the use of QAMZOVA in patients with severe heart failure unless the benefits are expected to outweigh the risk of worsening heart failure. If QAMZOVA is used in patients with severe heart failure, monitor patients for signs of worsening heart failure.

5.6 Renal Toxicity and Hyperkalemia

Renal Toxicity
Long-term administration of NSAIDs has resulted in renal papillary necrosis, renal insufficiency, acute renal failure, and other renal injury.

Renal toxicity has also been seen in patients in whom renal prostaglandins have a compensatory role in the maintenance of renal perfusion. In these patients, administration of an NSAID may cause a dose-dependent reduction in prostaglandin formation and, secondarily, in renal blood flow, which may precipitate overt renal decompensation. Patients at greatest risk of this reaction are those with impaired renal function, dehydration, hypovolemia, heart failure, liver dysfunction, those taking diuretics and ACE inhibitors or ARBs, and the elderly. Discontinuation of NSAID therapy is usually followed by recovery to the pretreatment state.

QAMZOVA is not recommended in patients with moderate to severe renal insufficiency and is contraindicated in patients with moderate to severe renal insufficiency who are at risk for renal failure due to volume depletion.

No information is available from controlled clinical studies regarding the use of QAMZOVA in patients with advanced renal disease. The renal effects of QAMZOVA may hasten the progression of renal dysfunction in patients with pre-existing renal disease.

Correct volume status in dehydrated or hypovolemic patients prior to initiating QAMZOVA. Monitor renal function in patients with renal or hepatic impairment, heart failure, dehydration, or hypovolemia during use of QAMZOVA [ see Drug Interactions (7) ]. Avoid the use of QAMZOVA in patients with advanced renal disease unless the benefits are expected to outweigh the risk of worsening renal function. If QAMZOVA is used in patients with advanced renal disease, monitor patients for signs of worsening renal function [ see Clinical Pharmacology (12.3) ].

Hyperkalemia
Increases in serum potassium concentration, including hyperkalemia, have been reported with use of NSAIDs, even in some patients without renal impairment. In patients with normal renal function, these effects have been attributed to a hyporeninemic-hypoaldosteronism state.

5.7 Anaphylactic Reactions

Meloxicam has been associated with anaphylactic reactions in patients with and without known hypersensitivity to meloxicam and in patients with aspirin-sensitive asthma [ see Contraindications (4) and Warnings and Precautions (5.8) ].

Seek emergency help if an anaphylactic reaction occurs.

5.8 Exacerbation of Asthma Related to Aspirin Sensitivity

A subpopulation of patients with asthma may have aspirin-sensitive asthma which may include chronic rhinosinusitis complicated by nasal polyps; severe, potentially fatal bronchospasm; and/or intolerance to aspirin and other NSAIDs. Because cross-reactivity between aspirin and other NSAIDs has been reported in such aspirin-sensitive patients, QAMZOVA is contraindicated in patients with this form of aspirin sensitivity [ see Contraindications (4) ]. When QAMZOVA is used in patients with preexisting asthma (without known aspirin sensitivity), monitor patients for changes in the signs and symptoms of asthma.

5.9 Serious Skin Reactions

NSAIDs, including QAMZOVA, can cause serious skin adverse events such as exfoliative dermatitis, Stevens-Johnson Syndrome (SJS), and toxic epidermal necrolysis (TEN), which can be fatal. These serious events may occur without warning. Patients should be informed about the signs and symptoms of serious skin manifestations and use of the drug should be discontinued at the first appearance of skin rash or any other sign of hypersensitivity. QAMZOVA is contraindicated in patients with previous serious skin reactions to NSAIDs [ see Contraindications (4) ].

5.10 Drug Reaction with Eosinophilia and Systemic Symptoms (DRESS)

Drug Reaction with Eosinophilia and Systemic Symptoms (DRESS) has been reported in patients taking NSAIDs such as QAMZOVA. Some of these events have been fatal or life-threatening. DRESS typically, although not exclusively, presents with fever, rash, lymphadenopathy, and/or facial swelling. Other clinical manifestations may include hepatitis, nephritis, hematological abnormalities, myocarditis, or myositis. Sometimes symptoms of DRESS may resemble an acute viral infection. Eosinophilia is often present. Because this disorder is variable in its presentation, other organ systems not noted here may be involved. It is important to note that early manifestations of hypersensitivity, such as fever or lymphadenopathy, may be present even though rash is not evident. If such signs or symptoms are present, discontinue QAMZOVA and evaluate the patient immediately.

5.11 Fetal Toxicity

Premature Closure of Fetal Ductus Arteriosus

Avoid use of NSAIDs, including QAMZOVA, in pregnant women at about 30 weeks gestation and later. NSAIDs, including QAMZOVA, increase the risk of premature closure of the fetal ductus arteriosus at approximately this gestational age.

Oligohydramnios/Neonatal Renal Impairment

Use of NSAIDs, including QAMZOVA, at about 20 weeks gestation or later in pregnancy may cause fetal renal dysfunction leading to oligohydramnios and, in some cases, neonatal renal impairment. These adverse outcomes are seen, on average, after days to weeks of treatment, although oligohydramnios has been infrequently reported as soon as 48 hours after NSAID initiation. Oligohydramnios is often, but not always, reversible with treatment discontinuation. Complications of prolonged oligohydramnios may, for example, include limb contractures and delayed lung maturation. In some postmarketing cases of impaired neonatal renal function, invasive procedures such as exchange transfusion or dialysis were required.

If NSAID treatment is necessary between about 20 weeks and 30 weeks gestation, limit QAMZOVA use to the lowest effective dose and shortest duration possible. Consider ultrasound monitoring of amniotic fluid if QAMZOVA treatment extends beyond 48 hours. Discontinue QAMZOVA if oligohydramnios occurs and follow up according to clinical practice [ see Use in Specific Populations (8.1) ]

5.12 Hematologic Toxicity

Anemia has occurred in NSAID-treated patients. This may be due to occult or gross blood loss, fluid retention, or an incompletely described effect on erythropoiesis. If a patient treated with QAMZOVA has any signs or symptoms of anemia, monitor hemoglobin or hematocrit.

NSAIDs, including QAMZOVA, may increase the risk of bleeding events. Co-morbid conditions such as coagulation disorders or concomitant use of warfarin, other anticoagulants, antiplatelet agents (e.g., aspirin), serotonin reuptake inhibitors (SSRIs) and serotonin norepinephrine reuptake inhibitors (SNRIs) may increase this risk. Monitor these patients for signs of bleeding [ see Drug Interactions (7) ].

5.13 Masking of Inflammation and Fever

The pharmacological activity of QAMZOVA in reducing inflammation, and possibly fever, may diminish the utility of diagnostic signs in detecting infections.

5.14 Laboratory Monitoring

Because serious GI bleeding, hepatotoxicity, and renal injury can occur without warning symptoms or signs, consider monitoring patients on long-term NSAID treatment with a CBC and a chemistry profile periodically [ see Warnings and Precautions (5.2, 5.3, 5.6) ]. QAMZOVA is not indicated for long-term treatment.

6 ADVERSE REACTIONS

The following adverse reactions are discussed in greater detail in the other sections of the labeling:

- Cardiovascular Thrombotic Events [ see Warnings and Precautions (5.1) ]
- GI Bleeding, Ulceration, and Perforation [ see Warnings and Precautions (5.2) ]
- Hepatotoxicity [ see Warnings and Precautions (5.3) ]
- Hypertension [ see Warnings and Precautions (5.4) ]
- Heart Failure and Edema [ see Warnings and Precautions (5.5) ]
- Renal Toxicity and Hyperkalemia [ see Warnings and Precautions (5.6) ]
- Anaphylactic Reactions [ see Warnings and Precautions (5.7) ]
- Serious Skin Reactions [ see Warnings and Precautions (5.9) ]
- Hematologic Toxicity [ see Warnings and Precautions (5.12)]

6.1 Clinical Trials Experience

Because clinical trials are conducted under widely varying conditions, adverse reaction rates observed in the clinical trials of a drug cannot be directly compared to rates in the clinical trials of another drug and may not reflect the rates observed in practice.

During clinical development, 1426 patients were exposed to meloxicam injection in controlled and open-label Phase 2 and Phase 3 trials. Meloxicam injection was studied across a range of surgical procedures, including bunionectomy, abdominoplasty, soft tissue surgery, total knee replacement surgery, gynecologic surgery, complex foot surgery and total hip replacement surgery. In these trials, 381 patients received a single dose of meloxicam injection and 1045 patients received multiple doses of meloxicam injection daily for up to 7 days. The incidence rates of adverse reactions listed in Table 1 are derived from the three Phase 3 trials comparing meloxicam injection to placebo in patients who may have also received opioid rescue medication.

Table 1: Proportion of Patients Experiencing Common Adverse Reactions in Placebo-Controlled Phase 3 Clinical Trials occurring in greater than or equal to 2% of Patients Treated with Meloxicam Injection and at a greater frequency than Placebo
 | Meloxicam Injection | Placebo
Adverse Reaction | N=748 | N=393
Constipation | 57 (7.6%) | 24 (6.1%)
Gamma-Glutamyl transferase Increased | 21 (2.8%) | 6 (1.5%)
Anemia | 18 (2.4%) | 4 (1.0%)

The following is a list of adverse drug reactions occurring in <2% of patients receiving meloxicam injection in clinical trials.

Table 2: Additional Adverse Reactions for Meloxicam Injection
Body as a Whole | asthenia, back pain, edema, fatigue, hyperthermia, infusion site reactions (including pain, pruritus, phlebitis and thrombosis), muscle spasms, noncardiac chest pain, pyrexia, vaginal discharge, weight decrease
Central and Peripheral Nervous System | disturbance in attention, migraine, presyncope, somnolence, syncope
Gastrointestinal | abdominal discomfort, abdominal distension, abdominal pain, diarrhea, dry mouth, epigastric discomfort, flatulence, frequent bowel movements, gastritis, gastroesophageal reflux, gastrointestinal pain, rectal hemorrhage
Heart Rate and Rhythm | tachycardia
Hematologic | increased bleeding time, neutropenia, thrombocytosis
Infections and Infestations | cellulitis, gastroenteritis, urinary tract infection, vulval abscess
Liver and Biliary System | liver function test abnormal
Metabolic and Nutritional | hypokalemia, hypomagnesemia
Procedural Complications | incision site hemorrhage, incision site rash, wound dehiscence, wound hematoma
Psychiatric | confusion, hallucination, insomnia
Respiratory | dyspnea, epistaxis, hypoxia, oropharyngeal pain
Skin and Appendages | contact dermatitis, ecchymosis, rash
Urinary System | pollakiuria, urinary retention

6.2 Postmarketing Experience

The following adverse reactions have been identified during postapproval use of meloxicam. Because these reactions are reported voluntarily from a population of uncertain size, it is not always possible to reliably estimate their frequency or establish a causal relationship to drug exposure.

Adverse reactions reported in worldwide post marketing experience or the literature include: acute urinary retention; agranulocytosis; alterations in mood (such as mood elevation); anaphylactoid reactions including shock; erythema multiforme; exfoliative dermatitis; interstitial nephritis; jaundice; liver failure; Stevens-Johnson syndrome; toxic epidermal necrolysis, and infertility female.

7 DRUG INTERACTIONS

See Table 3 for clinically significant drug interactions with meloxicam.

Table 3: Clinically Significant Drug Interactions with Meloxicam
Drugs That Interfere with Hemostasis
Clinical Impact: | - Meloxicam and anticoagulants such as warfarin have a synergistic effect on bleeding. The concomitant use of meloxicam and anticoagulants have an increased risk of serious bleeding compared to the use of either drug alone. - Serotonin release by platelets plays an important role in hemostasis. Case-control and cohort epidemiological studies showed that concomitant use of drugs that interfere with serotonin reuptake and an NSAID may potentiate the risk of bleeding more than an NSAID alone.
Intervention: | Monitor patients with concomitant use of QAMZOVA with anticoagulants (e.g., warfarin), antiplatelet agents (e.g., aspirin), selective serotonin reuptake inhibitors (SSRIs), and serotonin norepinephrine reuptake inhibitors (SNRIs) for signs of bleeding [ see Warnings and Precautions (5.12) ].
Aspirin
Clinical Impact: | Controlled clinical studies showed that the concomitant use of NSAIDs and analgesic doses of aspirin does not produce any greater therapeutic effect than the use of NSAIDs alone. In a clinical study, the concomitant use of an NSAID and aspirin was associated with a significantly increased incidence of GI adverse reactions as compared to use of the NSAID alone [ see Warnings and Precautions (5.2) ].
Intervention: | Concomitant use of QAMZOVA and analgesic doses of aspirin is not generally recommended because of the increased risk of bleeding [ see Warnings and Precautions (5.12) ]. In the setting of concomitant use of low-dose aspirin for cardiac prophylaxis, monitor patients more closely for evidence of GI bleeding [ see Warnings and Precautions (5.2) ]. QAMZOVA is not a substitute for low dose aspirin for cardiovascular protection.
ACE Inhibitors, Angiotensin Receptor Blockers, and Beta-Blockers
Clinical Impact: | - NSAIDs may diminish the antihypertensive effect of angiotensin converting enzyme (ACE) inhibitors, angiotensin receptor blockers (ARBs), or beta-blockers (including propranolol). - In patients who are elderly, volume-depleted (including those on diuretic therapy), or have renal impairment, co-administration of an NSAID with ACE inhibitors or ARBs may result in deterioration of renal function, including possible acute renal failure. These effects are usually reversible.
Intervention: | - During concomitant use of QAMZOVA and ACE-inhibitors, ARBs, or beta-blockers, monitor blood pressure to ensure that the desired blood pressure is obtained. - During concomitant use of QAMZOVA and ACE-inhibitors or ARBs in patients who are elderly, volume-depleted, or have impaired renal function, monitor for signs of worsening renal function [ see Warnings and Precautions (5.6) ]. - When these drugs are administered concomitantly, patients should be adequately hydrated. Assess renal function at the beginning of the concomitant treatment and periodically thereafter.
Diuretics
Clinical Impact: | Clinical studies, as well as post-marketing observations, showed that NSAIDs reduced the natriuretic effect of loop diuretics (e.g., furosemide) and thiazide diuretics in some patients. This effect has been attributed to the NSAID inhibition of renal prostaglandin synthesis. However, studies with furosemide agents and meloxicam have not demonstrated a reduction in natriuretic effect. Furosemide single and multiple dose pharmacodynamics and pharmacokinetics are not affected by multiple doses of meloxicam.
Intervention: | During concomitant use of QAMZOVA with diuretics, observe patients for signs of worsening renal function, in addition to assuring diuretic efficacy including antihypertensive effects [ see Warnings and Precautions (5.6) ].
Lithium
Clinical Impact: | NSAIDs have produced elevations in plasma lithium levels and reductions in renal lithium clearance. The mean minimum lithium concentration increased 15%, and the renal clearance decreased by approximately 20%. This effect has been attributed to NSAID inhibition of renal prostaglandin synthesis [ see Clinical Pharmacology (12.3) ].
Intervention: | During concomitant use of QAMZOVA and lithium, monitor patients for signs of lithium toxicity.
Methotrexate
Clinical Impact: | Concomitant use of NSAIDs and methotrexate may increase the risk for methotrexate toxicity (e.g., neutropenia, thrombocytopenia, renal dysfunction).
Intervention: | During concomitant use of QAMZOVA and methotrexate, monitor patients for methotrexate toxicity.
Cyclosporine
Clinical Impact: | Concomitant use of QAMZOVA and cyclosporine may increase cyclosporine’s nephrotoxicity.
Intervention: | During concomitant use of QAMZOVA and cyclosporine, monitor patients for signs of worsening renal function.
NSAIDs and Salicylates
Clinical Impact: | Concomitant use of meloxicam with other NSAIDs or salicylates (e.g., diflunisal, salsalate) increases the risk of GI toxicity, with little or no increase in efficacy [ see Warnings and Precautions (5.2) ].
Intervention: | The concomitant use of meloxicam with other NSAIDs or salicylates is not recommended.
Pemetrexed
Clinical Impact: | Concomitant use of QAMZOVA and pemetrexed may increase the risk of pemetrexed-associated myelosuppression, renal, and GI toxicity (see the pemetrexed prescribing information).
Intervention: | During concomitant use of QAMZOVA and pemetrexed, in patients with renal impairment whose creatinine clearance ranges from 45 to 79 mL/min, monitor for myelosuppression, renal and GI toxicity.; Patients taking meloxicam should interrupt dosing for at least five days before, the day of, and two days following pemetrexed administration.; In patients with creatinine clearance below 45 mL/min, the concomitant administration of meloxicam with pemetrexed is not recommended.
CYP2C9 Inhibitors
Clinical Impact: | In vitrostudies indicate that CYP2C9 (cytochrome P450 metabolizing enzyme) plays an important role in this metabolic pathway with a minor contribution of the CYP3A4 isozyme. Thus concomitant usage of CYP2C9 inhibitors (such as amiodarone, fluconazole, and sulphaphenazole) may lead to abnormally high plasma levels of meloxicam due to reduced metabolic clearance [ see Use in Specific Populations (8.8); and Clinical Pharmacology (12.3, 12.5) ].
Intervention: | Consider dose reduction in patients undergoing treatment with CYP2C9 inhibitors, and monitor patients for adverse effects.

8 USE IN SPECIFIC POPULATIONS

8.1 Pregnancy

Risk Summary

Use of NSAIDs, including QAMZOVA, can cause premature closure of the fetal ductus arteriosus and fetal renal dysfunction leading to oligohydramnios and, in some cases, neonatal renal impairment. Because of these risks, limit dose and duration of QAMZOVA use between about 20 and 30 weeks of gestation, and avoid QAMZOVA use at about 30 weeks of gestation and later in pregnancy (see Clinical Considerations, Data).

Premature Closure of Fetal Ductus Arteriosus

Use of NSAIDs, including QAMZOVA, at about 30 weeks gestation or later in pregnancy increases the risk of premature closure of the fetal ductus arteriosus.

Oligohydramnios/Neonatal Renal Impairment

Use of NSAIDs at about 20 weeks gestation or later in pregnancy has been associated with cases of fetal renal dysfunction leading to oligohydramnios, and in some cases, neonatal renal impairment.

Data from observational studies regarding potential embryofetal risks of NSAID use in women in the first or second trimesters of pregnancy are inconclusive.

In animal reproduction studies, embryofetal death was observed in rats and rabbits treated during the period of organogenesis with meloxicam at oral doses equivalent to 0.32- and 3.24-times the maximum recommended human dose (MRHD) of 30 mg of QAMZOVA. Increased incidence of septal heart defects were observed in rabbits treated throughout embryogenesis with meloxicam at an oral dose equivalent to 39-times the MRHD. In pre- and post-natal reproduction studies, there was an increased incidence of dystocia, delayed parturition, and decreased offspring survival at 0.04-times the MRHD. No teratogenic effects were observed in rats and rabbits treated with meloxicam during organogenesis at an oral dose equivalent to 1.3- and 13-times the MRHD [ see Data].

Based on animal data, prostaglandins have been shown to have an important role in endometrial vascular permeability, blastocyst implantation, and decidualization. In animal studies, administration of prostaglandin synthesis inhibitors, such as meloxicam, resulted in increased pre- and post-implantation loss. Prostaglandins also have been shown to have an important role in fetal kidney development. In published animal studies, prostaglandin synthesis inhibitors have been reported to impair kidney development when administered at clinically relevant doses.

The estimated background risk of major birth defects and miscarriage for the indicated population(s) is unknown. All pregnancies have a background risk of birth defect, loss, or other adverse outcomes. In the U.S. general population, the estimated background risk of major birth defects and miscarriage in clinically recognized pregnancies is 2% to 4% and 15% to 20%, respectively.

Clinical Considerations

Fetal/Neonatal Adverse Reactions

Premature Closure of Fetal Ductus Arteriosus:

Avoid use of NSAIDs in women at about 30 weeks gestation and later in pregnancy, because NSAIDs, including QAMZOVA, can cause premature closure of the fetal ductus arteriosus [ see Data].

Oligohydramnios/Neonatal Renal Impairment:

If an NSAID is necessary at about 20 weeks gestation or later in pregnancy, limit the use to the lowest effective dose and shortest duration possible. If QAMZOVA treatment extends beyond 48 hours, consider monitoring with ultrasound for oligohydramnios. If oligohydramnios occurs, discontinue QAMZOVA and follow up according to clinical practice [ see Data].

Labor or delivery

There are no studies on the effects of meloxicam during labor or delivery. In animal studies, NSAIDs, including meloxicam, inhibit prostaglandin synthesis, cause delayed parturition, and increase the incidence of stillbirth.

Data

Human Data

Premature Closure of Fetal Ductus Arteriosus:

Published literature reports that the use of NSAIDs at about 30 weeks of gestation and later in pregnancy may cause premature closure of the fetal ductus arteriosus.

Oligohydramnios/Neonatal Renal Impairment:

Published studies and postmarketing reports describe maternal NSAID use at about 20 weeks gestation or later in pregnancy associated with fetal renal dysfunction leading to oligohydramnios, and in some cases, neonatal renal impairment. These adverse outcomes are seen, on average, after days to weeks of treatment, although oligohydramnios has been infrequently reported as soon as 48 hours after NSAID initiation. In many cases, but not all, the decrease in amniotic fluid was transient and reversible with cessation of the drug. There have been a limited number of case reports of maternal NSAID use and neonatal renal dysfunction without oligohydramnios, some of which were irreversible. Some cases of neonatal renal dysfunction required treatment with invasive procedures, such as exchange transfusion or dialysis.

Methodological limitations of these postmarketing studies and reports include lack of a control group; limited information regarding dose, duration, and timing of drug exposure; and concomitant use of other medications. These limitations preclude establishing a reliable estimate of the risk of adverse fetal and neonatal outcomes with maternal NSAID use. Because the published safety data on neonatal outcomes involved mostly preterm infants, the generalizability of certain reported risks to the full-term infant exposed to NSAIDs through maternal use is uncertain.

Animal Data

Meloxicam was not teratogenic when administered to pregnant rats during fetal organogenesis at oral doses up to 4 mg/kg/day (1.3-times the MRHD of 30 mg based on body surface area (BSA) comparison). Administration of meloxicam to pregnant rabbits throughout embryogenesis produced an increased incidence of septal defects of the heart at an oral dose of 60 mg/kg/day (39-times the MRHD based on BSA comparison). The no effect level was 20 mg/kg/day (13-times the MRHD based on BSA comparision). In rats and rabbits, embryolethality occurred at oral meloxicam doses of 1 mg/kg/day and 5 mg/kg/day, respectively (0.32- and 3.24-times, respectively, the MRHD based on BSA comparison) when administered throughout organogenesis.

Oral administration of meloxicam to pregnant rats during late gestation through lactation increased the incidence of dystocia, delayed parturition, and decreased offspring survival at meloxicam doses of 0.125 mg/kg/day or greater (0.04-times the MRHD based on BSA comparison).

8.2 Lactation

Risk Summary

There are no human data available on whether meloxicam is present in human milk, or on the effects on breastfed infants, or on milk production. The developmental and health benefits of breastfeeding should be considered along with the mother’s clinical need for QAMZOVA and any potential adverse effects on the breastfed infant from the QAMZOVA or from the underlying maternal condition.

Data

Animal Data

Meloxicam was present in the milk of lactating rats at concentrations higher than those in plasma.

8.3 Females and Males of Reproductive Potential

Infertility

Females

Based on the mechanism of action, the use of prostaglandin-mediated NSAIDs, including QAMZOVA, may delay or prevent rupture of ovarian follicles, which has been associated with reversible infertility in some women. Published animal studies have shown that administration of prostaglandin synthesis inhibitors has the potential to disrupt prostaglandin-mediated follicular rupture required for ovulation. Small studies in women treated with NSAIDs have also shown a reversible delay in ovulation. Consider withdrawal of NSAIDs, including QAMZOVA, in women who have difficulties conceiving or who are undergoing investigation of infertility.

Males

QAMZOVA may compromise fertility in males of reproductive potential. In a published study, oral administration of meloxicam to male rats for 35 days resulted in decreased sperm count and motility and histopathological evidence of testicular degeneration at 0.3-times the MRHD based on BSA comparison [ see Nonclinical Toxicology (13.1) ]. It is not known if these effects on fertility are reversible. The clinical relevance of these findings is unknown.

8.4 Pediatric Use

The safety and efficacy of QAMZOVA has not been established in pediatric patients.

8.5 Geriatric Use

Elderly patients, compared to younger patients, are at greater risk for NSAID-associated serious cardiovascular, gastrointestinal, and/or renal adverse reactions. If the anticipated benefit for the elderly patient outweighs these potential risks monitor patients for adverse effects [ see Warnings and Precautions (5.1, 5.2, 5.3, 5.6, 5.14) ].

Of the total number of patients in clinical studies of meloxicam injection, 197 patients were age 65 and over. No overall differences in safety or effectiveness were observed between these patients and younger patients, and other reported clinical experience has not identified differences in responses between the elderly and younger patients.

8.6 Hepatic Impairment

QAMZOVA has not been studied in patients with hepatic impairment. For oral meloxicam, no dose adjustment is necessary in patients with mild to moderate hepatic impairment. Since meloxicam is significantly metabolized in the liver and hepatotoxicity may occur, monitor for adverse events in patients with severe hepatic impairment [ see Warnings and Precautions (5.3) and Clinical Pharmacology (12.3) ].

8.7 Renal Impairment

Pharmacokinetics of meloxicam injection in elderly subjects with mild renal impairment is similar to healthy young subjects. Patients with moderate or severe renal impairment have not been studied. QAMZOVA is not recommended in patients with moderate to severe renal insufficiency. QAMZOVA is contraindicated in patients with moderate to severe renal insufficiency who are at risk for renal failure due to volume depletion [ see Contraindications (4), Warnings and Precautions (5.6) and Clinical Pharmacology (12.3) ].

8.8 Poor Metabolizers of CYP2C9 Substrates

In patients who are known or suspected to be poor CYP2C9 metabolizers based on genotype or previous history/experience with other CYP2C9 substrates (such as warfarin and phenytoin) consider dose reduction as they may have abnormally high plasma levels due to reduced metabolic clearance, and monitor patients for adverse effects.

10 OVERDOSAGE

Symptoms following acute NSAID overdoses have been typically limited to lethargy, drowsiness, nausea, vomiting, and epigastric pain, which have been generally reversible with supportive care. Gastrointestinal bleeding has occurred. Hypertension, acute renal failure, respiratory depression and coma have occurred, but were rare [ see Warnings and Precautions (5.1, 5.2, 5.4, 5.6) ].

Manage patients with symptomatic and supportive care following an NSAID overdosage. There are no specific antidotes. Forced diuresis, alkalinization of urine, hemodialysis, or hemoperfusion may be employed but are not likely to be useful due to high protein binding.

There is limited experience with meloxicam overdose. In four reported cases of meloxicam overdose, patients took 6 to 11 times the highest available oral dose of meloxicam tablets (15 mg); all recovered. Cholestyramine is known to accelerate the clearance of meloxicam. Accelerated removal of meloxicam by 4 g doses of cholestyramine given three times a day was demonstrated in a clinical trial. Administration of cholestyramine may be useful following an overdosage.

In case of an overdosage, discontinue QAMZOVA therapy and contact a regional poison control center at 1-800-222-1222.

11 DESCRIPTION

QAMZOVA contains meloxicam, which is a nonsteroidal anti-inflammatory drug (NSAID). It is a sterile clear, greenish-yellow, aqueous solution containing the active pharmaceutical ingredient meloxicam for intravenous administration. Each mL of aqueous solution contains 30 mg of meloxicam and 300 mg of polyethylene glycol 400 in water for injection. The pH of the solution is adjusted with sodium hydroxide and citric acid monohydrate if necessary. The solution pH ranges from 7.4 to 8.4.

Meloxicam is a pale yellow powder, practically insoluble in water, slightly soluble in acetone, soluble in dimethylformamide, and very slightly soluble in methanol and in alcohol. Meloxicam is designated chemically as 4-hydroxy-2-methyl-N-(5-methyl-2-thiazolyl)-2H-1,2- benzothiazine-3-carboxamide-1,1-dioxide. The molecular weight is 351.4. Its molecular formula is C14H13N3O4S2 and the structural formula of meloxicam is:

Figure 1: Structural Formula of Meloxicam

12 CLINICAL PHARMACOLOGY

12.1 Mechanism of Action

Meloxicam has analgesic, anti-inflammatory, and antipyretic properties.

The mechanism of action of meloxicam, like that of other NSAIDs, is not completely understood but involves inhibition of cyclooxygenase (COX-1 and COX-2).

Meloxicam is a potent inhibitor of prostaglandin synthesis in vitro. Meloxicam concentrations reached during therapy have produced in vivoeffects. Prostaglandins sensitize afferent nerves and potentiate the action of bradykinin in inducing pain in animal models. Prostaglandins are mediators of inflammation. Because meloxicam is an inhibitor of prostaglandin synthesis, its mode of action may be due to a decrease of prostaglandins in peripheral tissues.

12.2 Pharmacodynamics

Cardiac Electrophysiology

The effect of meloxicam injection on QTc prolongation was evaluated in a randomized, double-blind, placebo-controlled crossover study in healthy subjects. A total of 48 subjects were administered intravenous meloxicam 30 mg, 120 mg, and 180 mg. In a study with demonstrated ability to detect small effects, the upper bound of the 90% confidence interval for the largest placebo-adjusted, baseline- corrected QTc based on Fridericia correction method (QTcF) was below 10 ms, the threshold for regulatory concern.

12.3 Pharmacokinetics

Absorption

Following intravenous administration of meloxicam injection to healthy volunteers, plasma concentrations of 30 mg meloxicam injection exceed that of 15 mg oral meloxicam for the first 24 hours. The single-dose pharmacokinetics of meloxicam following intravenous administration of QAMZOVA are presented in Table 4.

Table 4: Single-Dose Pharmacokinetics of QAMZOVA Injection
 | QAMZOVA
 | 30 mg IV
Parameter
Cmax(ng/mL) | 6667.2±984.0
Tmax(h) | 0.10±0.04
AUCinf(ng*hr/mL) | 102301.5±31999.9
T½(h) | 21.1±6.2

Following multiple dosing, QAMZOVA is predicted to have slightly higher than 2-fold accumulation without a change in the terminal elimination half-life.

Meloxicam injection exhibits linear pharmacokinetics over intravenous doses ranging from 15 mg to 180 mg.

Distribution

Following administration of meloxicam injection, the apparent volume of distribution during the terminal elimination phase (Vz) of meloxicam is 9.63 L.

Meloxicam is ~99.4% bound to human plasma proteins (primarily albumin) within the therapeutic dose range. The fraction of protein binding is independent of drug concentration, over the clinically relevant concentration range, but decreases to ~99% in patients with renal disease. Meloxicam penetration into human red blood cells, after oral dosing, is less than 10%. Following a radiolabeled dose, over 90% of the radioactivity detected in the plasma was present as unchanged meloxicam.

Meloxicam concentrations in synovial fluid, after a single oral dose, range from 40% to 50% of those in plasma. The free fraction in synovial fluid is 2.5 times higher than in plasma, due to the lower albumin content in synovial fluid as compared to plasma. The significance of this penetration is unknown.

Elimination

Metabolism

Meloxicam is extensively metabolized in the liver. Meloxicam metabolites include 5'-carboxy meloxicam (60% of dose), from P-450 mediated metabolism formed by oxidation of an intermediate metabolite 5'-hydroxymethyl meloxicam which is also excreted to a lesser extent (9% of dose). In vitrostudies indicate that CYP2C9 (cytochrome P450 metabolizing enzyme) plays an important role in this metabolic pathway with a minor contribution of the CYP3A4 isozyme. Patients’ peroxidase activity is probably responsible for the other two metabolites which account for 16% and 4% of the administered dose, respectively. The four metabolites are not known to have any in vivopharmacological activity.

Excretion

Meloxicam excretion is predominantly in the form of metabolites, and occurs to equal extents in the urine and feces. Only traces of the unchanged parent compound are excreted in the urine (0.2%) and feces (1.6%). The extent of the urinary excretion was confirmed for unlabeled multiple 7.5 mg doses: 0.5%, 6%, and 13% of the dose were found in urine in the form of meloxicam, and the 5'-hydroxymethyl and 5'-carboxy metabolites, respectively. There is significant biliary and/or enteral secretion of the drug. This was demonstrated when oral administration of cholestyramine following a single IV dose of meloxicam decreased the AUC of meloxicam by 50%.

The mean elimination half-life (t1/2) for QAMZOVA 30 mg is approximately 21 hours.

Specific Populations

Based on population pharmacokinetics analyses, age, sex and race do not have a clinically meaningful effect on the PK of meloxicam injection.

Hepatic Impairment: The pharmacokinetics of QAMZOVA have not been investigated in patients with hepatic impairment. However, following a single 15 mg dose of meloxicam tablets there was no marked difference in plasma concentrations in patients with mild (Child-Pugh Class I) or moderate (Child-Pugh Class II) hepatic impairment compared to healthy volunteers. Protein binding of meloxicam was not affected by hepatic impairment. No dosage adjustment is necessary in patients with mild to moderate hepatic impairment. Patients with severe hepatic impairment (Child-Pugh Class III) have not been adequately studied. Monitor for adverse events when used in patients with severe hepatic impairment [ see Warnings and Precautions (5.3), Use in Specific Populations (8.6) ].

Renal Impairment: Meloxicam injection pharmacokinetics have been investigated in elderly subjects with mild renal impairment (eGFR 60 - 90) compared to young healthy volunteers. A 5% and 7% increase of Cmax and AUC, respectively, was observed in elderly subjects with mild renal impairment. No dosage adjustment is necessary in patients with mild renal impairment. Patients with moderate and severe renal impairment have not been adequately studied. The use of QAMZOVA in patients with moderate to severe renal impairment is not recommended. QAMZOVA is contraindicated in patients with moderate to severe renal insufficiency who are at risk for renal failure due to volume depletion [ see Contraindications (4), Warnings and Precautions (5.6), Use in Specific Populations (8.7) ].

Drug Interaction Studies

Aspirin: When NSAIDs were administered with aspirin, the protein binding of NSAIDs were reduced, although the clearance of free NSAID was not altered. The clinical significance of this interaction is not known. See Table 3clinically significant drug interactions of NSAIDs with aspirin [ see Drug Interactions (7) ].

Cholestyramine: Pretreatment for four days with cholestyramine significantly increased the clearance of meloxicam by 50%. This resulted in a decrease in t1/2, from 19.2 hours to 12.5 hours, and a 35% reduction in AUC. This suggests the existence of a recirculation pathway for meloxicam in the gastrointestinal tract. The clinical relevance of this interaction has not been established.

Cimetidine: Concomitant administration of 200 mg cimetidine four times daily did not alter the single-dose pharmacokinetics of 30 mg meloxicam.

Digoxin: Meloxicam tablets 15 mg once daily for 7 days did not alter the plasma concentration profile of digoxin after β-acetyldigoxin administration for 7 days at clinical doses. In vitrotesting found no protein binding drug interaction between digoxin and meloxicam [ see Drug Interactions (7) ].

Lithium: In a study conducted in healthy subjects, mean pre-dose lithium concentration and AUC were increased by 21% in subjects receiving lithium doses ranging from 804 to 1072 mg twice daily with meloxicam tablets 15 mg once per day every day as compared to subjects receiving lithium alone [ see Drug Interactions (7) ].

Methotrexate: A study in 13 rheumatoid arthritis (RA) patients evaluated the effects of multiple oral doses of meloxicam on the pharmacokinetics of methotrexate taken once weekly. Meloxicam did not have a significant effect on the pharmacokinetics of single doses of methotrexate. In vitro, methotrexate did not displace meloxicam from its human serum binding sites [ see Drug Interactions (7) ].

Warfarin: The effect of meloxicam tablets on the anticoagulant effect of warfarin was studied in a group of healthy subjects receiving daily doses of warfarin that produced an INR (International Normalized Ratio) between 1.2 and 1.8. In these subjects, meloxicam did not alter warfarin pharmacokinetics and the average anticoagulant effect of warfarin as determined by prothrombin time. However, one subject showed an increase in INR from 1.5 to 2.1. Caution should be used when administering QAMZOVA with warfarin since patients on warfarin may experience changes in INR and an increased risk of bleeding complications when a new medication is introduced [ see Drug Interactions (7) ].

12.5 Pharmacogenomics

CYP2C9 activity is reduced in individuals with genetic variants such as CYP2C9*2 and CYP2C9*3 polymorphisms. Limited data from three published reports showed that meloxicam AUC was substantially higher in individuals with reduced CYP2C9 activity, particularly in poor metabolizers (e.g., *3/*3), compared to normal metabolizers (*1/*1). The frequency of CYP2C9 poor metabolizer genotypes varies based on racial/ethnic background but is generally present in <5% of the population.

13 NONCLINICAL TOXICOLOGY

13.1 Carcinogenesis, Mutagenesis, Impairment of Fertility

Carcinogenesis

There was no increase in tumor incidence in long-term carcinogenicity studies in rats (104 weeks) and mice (99 weeks) administered meloxicam at oral doses up to 0.8 mg/kg/day in rats and up to 8.0 mg/kg/day in mice (up to 0.26- and 1.3-times, respectively, the MRHD of 30 mg/day of QAMZOVA based on BSA comparison).

Mutagenesis

Meloxicam was not mutagenic in an Ames assay. Meloxicam was not clastogenic in a chromosome aberration assay with human lymphocytes and an in vivomicronucleus test in mouse bone marrow.

Impairment of Fertility

Meloxicam did not impair male and female fertility in rats at oral doses up to 9 mg/kg/day in males and 5 mg/kg/day in females (up to 2.9- and 1.6-times, respectively, the MRHD based on BSA comparison).

In a published study, oral administration of 1 mg/kg (0.3-times the MRHD based on BSA comparison) meloxicam to male rats for 35 days resulted in decreased sperm count and motility and histopathological evidence of testicular degeneration. The clinical relevance of these findings is unknown.

14 CLINICAL STUDIES

The efficacy and safety of meloxicam injection in the treatment of moderate to severe pain was evaluated in two Phase 3 randomized, double-blind, placebo-controlled, multiple-dose clinical trials in patients with postoperative pain. In both trials, oral oxycodone 5 mg was permitted as rescue medication for pain management.

Study 1 (Bunionectomy Surgery)

In the first controlled, multiple-dose trial (NCT02675907) of adult patients with postoperative pain who underwent bunionectomy surgery, 201 patients were treated with meloxicam injection 30 mg or placebo administered once daily for two days starting on the day after surgery. An optional third dose was permitted just prior to discharge. A minimum postoperative baseline pain intensity of 4 on the Numeric Pain Rating Scale (NPRS) (range 0-10) and pain categorized as moderate or severe were required for randomization. The majority of patients were female (85%). The average age was 48 years. The mean overall baseline pain intensity on the NPRS was 6.8. A statistically significant difference demonstrating efficacy was observed in the primary efficacy endpoint of the summed pain intensity difference over the first 48 hours (SPID48). The average pain intensity over time is depicted for the treatment groups in Figure 2. A generally consistent separation in pain scores between meloxicam injection and placebo groups was observed from time of onset through most of the dosing interval with a narrowing at the end of the first 24-hour dosing interval.

Figure 2

Study 2 (Abdominoplasty Surgery)

In the second controlled, multiple-dose trial (NCT02678286) of adult patients with postoperative pain who underwent elective abdominoplasty surgery, 219 patients were treated with meloxicam injection 30 mg or placebo administered once daily for two days starting on the day of surgery. An optional third dose was permitted just prior to discharge. A minimum postoperative baseline pain intensity of 4 on the NPRS (range 0-10) and pain categorized as moderate or severe were required for randomization. The majority of patients were female (98%). The average age was 40 years. The mean overall baseline pain intensity on the NPRS was 7.3. A statistically significant difference demonstrating efficacy was observed in the primary efficacy endpoint of the summed pain intensity difference over the first 24 hours (SPID24) as well as over the first 48 hours (SPID48). The average pain intensity over time is depicted for the treatment groups in Figure 3. A generally consistent separation in pain scores between the meloxicam injection and placebo group was observed from time of onset through most of the dosing interval with a narrowing at the end of the first 24-hour dosing interval.

Figure 3

Onset of Meaningful Pain Relief and Use of Rescue Analgesic Medication

The median time to first rescue analgesic use in patients treated with meloxicam injection (2 hours in Study 1 and 1 hour in Study 2) came before the median time to patient-reported meaningful pain relief in both studies (2 hours in Study 1 and 3 hours in Study 2). Fifty percent of patients treated with meloxicam injection and 49% of patients treated with placebo in Study 1 received rescue analgesia medication in the first 2 hours after the start of dosing. Seventy-eight percent of patients treated with meloxicam injection and 78% of patients treated with placebo in Study 2 received rescue in the first 3 hours after the start of dosing.

16 HOW SUPPLIED/STORAGE AND HANDLING

QAMZOVA (meloxicam) injection, is a clear, greenish-yellow aqueous solution intended for intravenous use supplied as a 1 mL fill (30 mg/mL) in a clear single-dose vial with a blue flip-off cap.

Single-dose vial: NDC 82972-001-30

STORAGE AND HANDLING

Store at 20°C to 25°C (68°F to 77°F), with excursions permitted to 15°C to 30°C (59°F to 86°F) [see USP Controlled Room Temperature].

Do not freeze. Protect from light.

Discard unused portion.

17 PATIENT COUNSELING INFORMATION

Inform patients of the following information before initiating therapy with QAMZOVA.

Cardiovascular Thrombotic Effects

Advise patients to be alert for the symptoms of cardiovascular thrombotic events, including chest pain, shortness of breath, weakness, or slurring of speech, and to report any of these symptoms to their healthcare provider immediately[ see Warnings and Precautions (5.1) ].

Gastrointestinal Bleeding, Ulceration, and Perforation

Advise patients to report symptoms of ulcerations and bleeding, including epigastric pain, dyspepsia, melena, and hematemesis to their healthcare provider. In the setting of concomitant use of low-dose aspirin for cardiac prophylaxis, inform patients of the increased risk for the signs and symptoms of GI bleeding [ see Warnings and Precautions (5.2) ].

Hepatotoxicity

Inform patients of the warning signs and symptoms of hepatotoxicity (e.g., nausea, fatigue, lethargy, diarrhea, pruritus, jaundice, right upper quadrant tenderness, and "flu-like" symptoms). If these occur, instruct patients to stop QAMZOVA and seek immediate medical therapy [ see Warnings and Precautions (5.3) ].

Heart Failure and Edema

Advise patients to be alert for the symptoms of congestive heart failure including shortness of breath, unexplained weight gain, or edema and to contact their healthcare provider if such symptoms occur [ see Warnings and Precautions (5.5) ].

Anaphylactic Reactions

Inform patients of the signs of an anaphylactic reaction (e.g., difficulty breathing, swelling of the face or throat). Instruct patients to seek immediate emergency help if these occur [ see Contraindications (4) and Warnings and Precautions (5.7) ].

Serious Skin Reactions including DRESS

Advise patients to stop taking QAMZOVA immediately if they develop any type of rash or fever and to contact their healthcare provider as soon as possible [ see Warnings and Precautions (5.9, 5.10) ].

Female Fertility

Advise females of reproductive potential who desire pregnancy that NSAIDs, including QAMZOVA, may be associated with a reversible delay in ovulation [ see Use in Specific Populations (8.3) ].

Fetal Toxicity

Inform pregnant women to avoid use of QAMZOVA and other NSAIDs starting at 30 weeks gestation because of the risk of the premature closing of the fetal ductus arteriosus. If treatment with QAMZOVA is needed for a pregnant woman between about 20 to 30 weeks gestation, advise her that she may need to be monitored for oligohydramnios, if treatment continues for longer than 48 hours [ see Warnings and Precautions (5.11) and Use in Specific Populations (8.1) ].

Avoid Concomitant Use of NSAIDs

Inform patients that the concomitant use of QAMZOVA with other NSAIDs or salicylates (e.g., diflunisal, salsalate) is not recommended due to the increased risk of gastrointestinal toxicity, and little or no increase in efficacy [ see Warnings and Precautions (5.2) and Drug Interactions (7) ]. Alert patients that NSAIDs may be present in “over the counter” medications for treatment of colds, fever, or insomnia.

Use of NSAIDs and Low-Dose Aspirin

Inform patients not to use low-dose aspirin concomitantly with QAMZOVA until they talk to their healthcare provider [ see Drug Interactions (7) ].

This PRESCRIBING INFORMATION has been approved by the US Food and Drug Administration.

Manufactured for:

Nanjing Delova Biotech Co., Ltd.

Nanjing, Jiangsu 210042, China

Made in China

Prescribing Information issued: April 2025

PACKAGE LABEL

PRINCIPAL DISPLAY PANEL - NDC: 82972-001-30 - Vial Carton Label

PRINCIPAL DISPLAY PANEL - NDC: 82972-001-30 - Vial Label